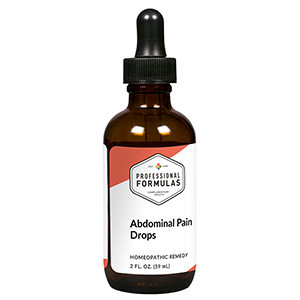 DRUG LABEL: Abdominal Pain Drops
NDC: 63083-2051 | Form: LIQUID
Manufacturer: Professional Complementary Health Formulas
Category: homeopathic | Type: HUMAN OTC DRUG LABEL
Date: 20190815

ACTIVE INGREDIENTS: ARTEMISIA ANNUA FLOWERING TOP 3 [hp_X]/59 mL; LYCOPODIUM CLAVATUM SPORE 5 [hp_X]/59 mL; ACTIVATED CHARCOAL 6 [hp_X]/59 mL; SODIUM SULFATE 6 [hp_X]/59 mL; BOS TAURUS SOLAR PLEXUS 6 [hp_X]/59 mL; TRIPE 6 [hp_X]/59 mL; SUS SCROFA PARASYMPATHETIC NERVE 6 [hp_X]/59 mL; HYDROCHLORIC ACID 12 [hp_X]/59 mL; STRYCHNOS NUX-VOMICA SEED 30 [hp_X]/59 mL
INACTIVE INGREDIENTS: ALCOHOL; WATER

C51

ACTIVE INGREDIENTS

Chamomilla 3X
Lycopodium clavatum 5X
Carbo vegetabilis 6X
Natrum sulphuricum 6X
Solar plexus 6X
Stomach 6X
Vagus nerve 6X
Muriaticum acidum 12X
Nux vomica 30X

QUESTIONS

Professional Formulas

PO Box 2034 Lake Oswego, OR 97035

INDICATIONS

For the temporary relief of mild abdominal pain, cramping, or spasms, bloating, or flatulence.*

PURPOSE

*Claims based on traditional homeopathic practice, not accepted medical evidence. Not FDA evaluated.

WARNINGS

In case of overdose, get medical help or contact a poison control center right away.

Keep out of the reach of children.

PREGNANCY OR BREAST FEEDING

If pregnant or breastfeeding, ask a healthcare professional before use.

DIRECTIONS

Place drops under tongue 30 minutes before/after meals. Adults and children 12 years and over: Take 10 drops up to 3 times per day for up to 6 weeks. For immediate onset of symptoms, take 10 to 15 drops every 15 minutes up to 3 hours. For less severe symptoms, take 10-15 drops hourly up to 8 hours. Consult a physician for use in children under 12 years of age.

OTHER INFORMATION

Tamper resistant. If seal is broken, do not use. After opening, close container tightly and store at room temperature away from heat.

INACTIVE INGREDIENTS

20% ethanol, purified water.

LABEL

Est 1985

Professional Formulas

Complementary Health

Abdominal Pain Drops

Homeopathic Remedy

2 FL. OZ. (59 mL)